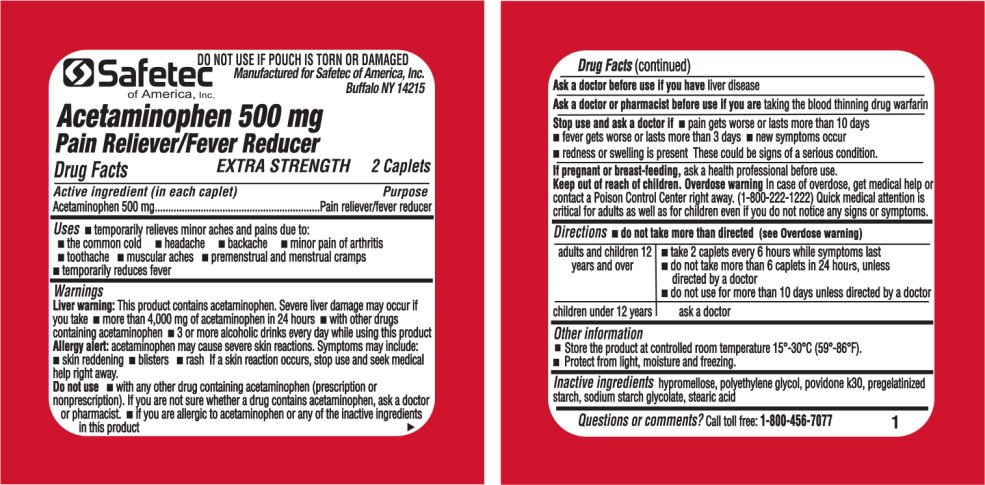 DRUG LABEL: Acetaminophen
NDC: 61010-4406 | Form: TABLET
Manufacturer: Safetec of America, Inc.
Category: otc | Type: HUMAN OTC DRUG LABEL
Date: 20191230

ACTIVE INGREDIENTS: Acetaminophen 500 mg/1 1
INACTIVE INGREDIENTS: hypromellose 2208 (15000 MPA.S); polyethylene glycol, unspecified; povidone k30; starch, corn; sodium starch glycolate type a potato; stearic acid

Drug Facts

Active ingredients (in each caplet)

Acetaminophen 500 mg

Purpose

Pain reliever/fever reducer

Uses

- Temporarily relieves minor aches and pains due to:
  - the common cold
  - headache
  - backache
  - minor pain of arthritis
  - toothache
  - muscular aches
  - premenstrual and menstrual cramps
- temporarily reduces fever

Warnings

Liver warning: This product contains acetaminophen. Severe liver damage may occur if you take

- more than 4,000 mg of acetaminophen in 24 hours
- with other drugs containing acetaminophen
- 3 or more alcoholic drinks every day while using this product

Allergy alert: acetaminophen may case Severe skin reactions. Symptoms may include:

- skin reddening
- blisters
- rash

If a skin reaction occurs, stop use and seek medical help right away.

Do not use

- with any other drug containing acetaminophen (prescription or nonprescription). If you are not sure whether a drug contains acetaminophen, ask a doctor or pharmacist.
- if you are allergic to acetaminophen or any of the inactive ingredients in this product

Ask a doctor before use if you have liver disease

Ask a doctor or pharmacist before use if you are taking the blood thinning drug warfarin

Stop use and ask a doctor if

- pain gets worse or last more than 10 days
- fever gets worse or lasts more than 3 days
- new symptoms occur
- redness or swelling is present

These could be signs of a serious condition.

PREGNANCY OR BREAST FEEDING

If pregnant or breast-feeding, ask a health professional before use.

Overdose warning

In case of overdose, get medical help or contact a Poison Control Center right away. (1-800-222-1222) Quick medical attention is critical for adults as well as for children even if you do not notice any signs or symptoms.

Directions

- do not take more than directed (see Overdose warning)

adults and children 12 years and over

- take 2 caplets every 6 hours while symptoms last
- do not take more than 6 caplets in 24 hours, unless directed by a doctor
- do not use for more than 10 days unless directed by a doctor

children under 12 years

ask a doctor

Other information

- Store the product at controlled room temperature 15°-30°C (59°-86°F).
- Protect from light, moisture and freezing.

Inactive ingredients

hypromellose, polyethylene glycol, povidone k30, pregelatinized starch, sodium starch glycolate, stearic acid.

Questions or comments?

Call toll free: 1-800-456-7077

Principal Display Panel – Pouch Label

DO NOT USE IF POUCH IS TORN OR DAMAGED

Safetec
of America, Inc.

Manufactured for Safetec of America, Inc.
Buffalo NY 14215

Acetaminophen 500 mg

Pain Reliever/Fever Reducer